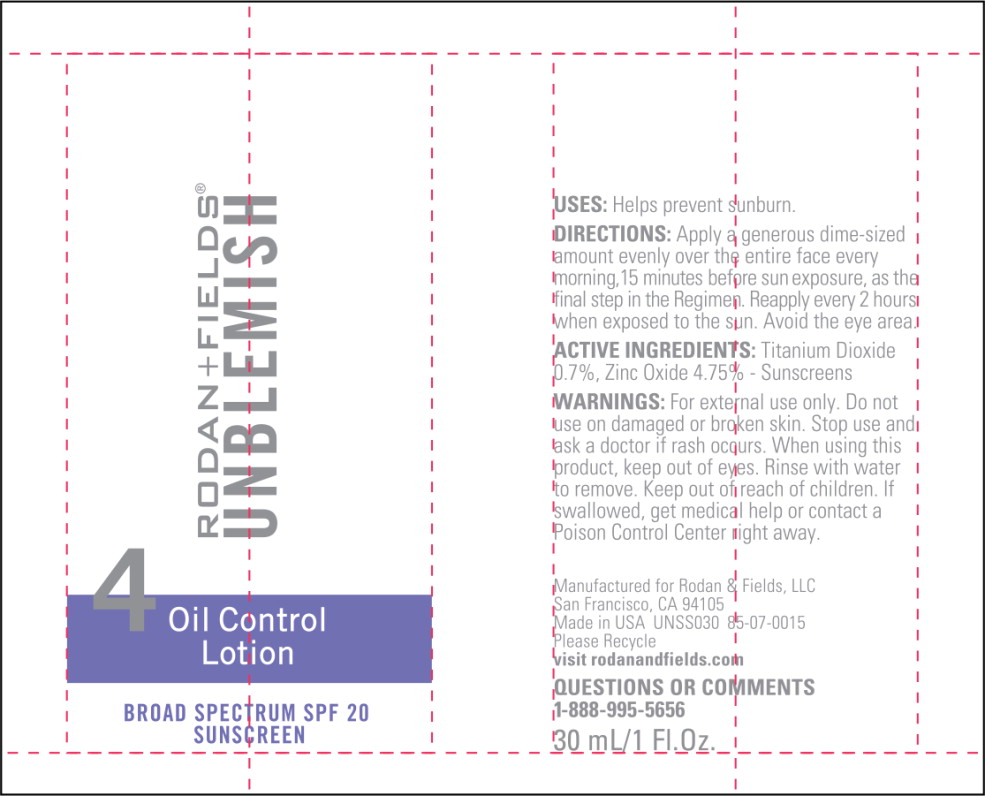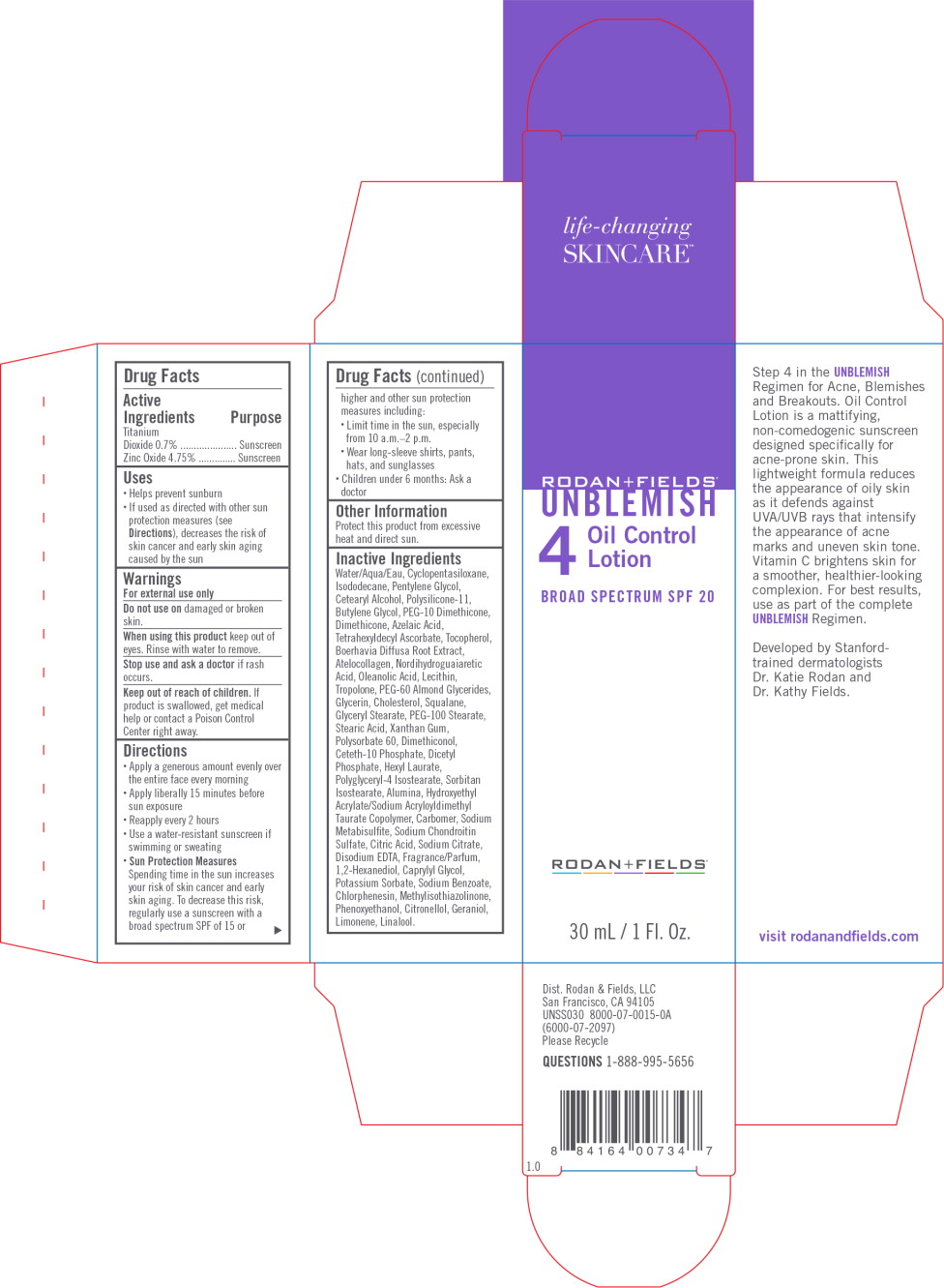 DRUG LABEL: UNBLEMISH Control Broad Spectrum SPF 20
NDC: 14222-2060 | Form: LOTION
Manufacturer: Rodan & Fields 
Category: otc | Type: HUMAN OTC DRUG LABEL
Date: 20171006

ACTIVE INGREDIENTS: Titanium Dioxide 0.7 g/100 mL; Zinc Oxide 4.75 g/100 mL
INACTIVE INGREDIENTS: Water; Cyclomethicone 5; Isododecane; Pentylene Glycol; Cetostearyl Alcohol; Dimethicone/Vinyl Dimethicone Crosspolymer (Soft Particle); Butylene Glycol; PEG-10 Dimethicone (600 CST); Dimethicone; Azelaic Acid; Tetrahexyldecyl Ascorbate; Tocopherol; Boerhavia Diffusa Root; Marine Collagen, Soluble; Nordihydroguaiaretic Acid, (+/-)-; Oleanolic Acid; Lecithin, Soybean; Tropolone; PEG-60 Almond Glycerides; Glycerin; Cholesterol; Squalane; Glyceryl Monostearate; PEG-100 Stearate; Stearic Acid; Xanthan Gum; Polysorbate 60; Dimethiconol (40 CST); Ceteth-10 Phosphate; Dihexadecyl Phosphate; Hexyl Laurate; Polyglyceryl-4 Isostearate; Sorbitan Isostearate; Aluminum Oxide; Hydroxyethyl Acrylate/Sodium Acryloyldimethyl Taurate Copolymer (100000 MPA.S At 1.5%); Carboxypolymethylene; Sodium Metabisulfite; Sodium Chondroitin Sulfate (Porcine; 5500 MW); Citric Acid Monohydrate; Sodium Citrate; Edetate Disodium Anhydrous; 1,2-Hexanediol; Caprylyl Glycol; Potassium Sorbate; Sodium Benzoate; Chlorphenesin; Methylisothiazolinone; Phenoxyethanol; .Beta.-Citronellol, (R)-; Geraniol; Limonene, (+)-; Linalool, (+/-)-

Drug Facts

Active Ingredients

Titanium Dioxide 0.7%

Zinc Oxide 4.75%

Purpose

Sunscreen

Sunscreen

Uses

- Helps prevent sunburn
- If used as directed with other sun protection measures (see Directions), decreases the risk of skin cancer and early skin aging caused by the sun

Warnings

For external use only

Do not use on damaged or broken skin.

When using this product keep out of eyes. Rinse with water to remove.

Stop use and ask a doctor if rash occurs.

Keep out of reach of children. If product is swallowed, get medical help or contact a Poison Control Center right away.

Directions

- Apply a generous amount evenly over the entire face every morning
- Apply liberally 15 minutes before sun exposure
- Reapply every 2 hours
- Use a water-resistant sunscreen if swimming or sweating
- Sun Protection Measures
  Spending time in the sun increases your risk of skin cancer and early skin aging. To decrease this risk, regularly use a sunscreen with a broad spectrum SPF of 15 or higher and other sun protection measures including:
  - Limit time in the sun, especially from 10 a.m.–2 p.m.
  - Wear long-sleeve shirts, pants, hats, and sunglasses
- Children under 6 months: Ask a doctor

Other Information

Protect this product from excessive heat and direct sun.

Inactive Ingredients

Water/Aqua/Eau, Cyclopentasiloxane, Isododecane, Pentylene Glycol, Cetearyl Alcohol, Polysilicone-11, Butylene Glycol, PEG-10 Dimethicone, Dimethicone, Azelaic Acid, Tetrahexyldecyl Ascorbate, Tocopherol, Boerhavia Diffusa Root Extract, Atelocollagen, Nordihydroguaiaretic Acid, Oleanolic Acid, Lecithin, Tropolone, PEG-60 Almond Glycerides, Glycerin, Cholesterol, Squalane, Glyceryl Stearate, PEG-100 Stearate, Stearic Acid, Xanthan Gum, Polysorbate 60, Dimethiconol, Ceteth-10 Phosphate, Dicetyl Phosphate, Hexyl Laurate, Polyglyceryl-4 Isostearate, Sorbitan Isostearate, Alumina, Hydroxyethyl Acrylate/Sodium Acryloyldimethyl Taurate Copolymer, Carbomer, Sodium Metabisulfite, Sodium Chondroitin Sulfate, Citric Acid, Sodium Citrate, Disodium EDTA, Fragrance/Parfum, 1,2-Hexanediol, Caprylyl Glycol, Potassium Sorbate, Sodium Benzoate, Chlorphenesin, Methylisothiazolinone, Phenoxyethanol, Citronellol, Geraniol, Limonene, Linalool.

Principal Display Panel - UNBLEMISH Oil Control Lotion Tube Label

RODAN+FIELDS®
UNBLEMISH

4

Oil Control
Lotion

BROAD SPECTRUM SPF 20
SUNSCREEN

Principal Display Panel - UNBLEMISH Oil Control Lotion Carton Label

RODAN+FIELDS®
UNBLEMISH

4

Oil Control
Lotion

BROAD SPECTRUM SPF 20

RODAN+FIELDS®

30 mL/1 Fl. Oz.